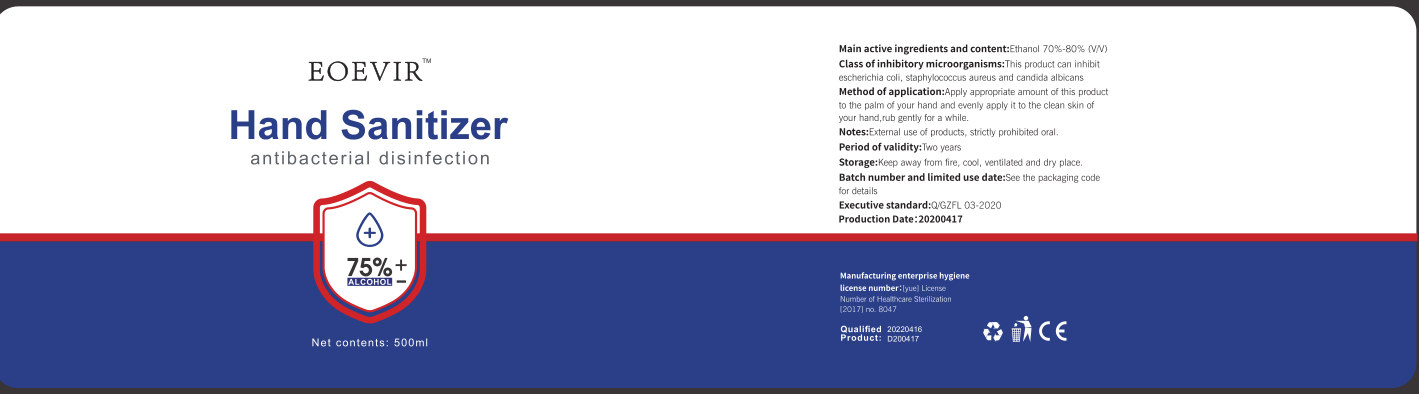 DRUG LABEL: hand sanitizer
NDC: 54493-003 | Form: LIQUID
Manufacturer: Shenzhen YJD Technology Co., Ltd.
Category: otc | Type: HUMAN OTC DRUG LABEL
Date: 20200426

ACTIVE INGREDIENTS: ALCOHOL 375 mL/500 mL
INACTIVE INGREDIENTS: TROLAMINE; WATER; GLYCERIN; CARBOMER HOMOPOLYMER, UNSPECIFIED TYPE

DOSAGE AND ADMINISTRATION

Keep away from fire, cool, ventilated and dry place.

INACTIVE INGREDIENT

Water

Glycerin

Carbomer

Triethanolamine

INDICATIONS AND USAGE

Apply appropriate amount of this product to the palm of your hand and evenly apply it to the clean skin of your hand,rub gently for a while.

ACTIVE INGREDIENT

Alcohol

PURPOSE

Disinfection
Sterilization

keep out of children

WARNINGS

External use of products, strictly prohibited oral.